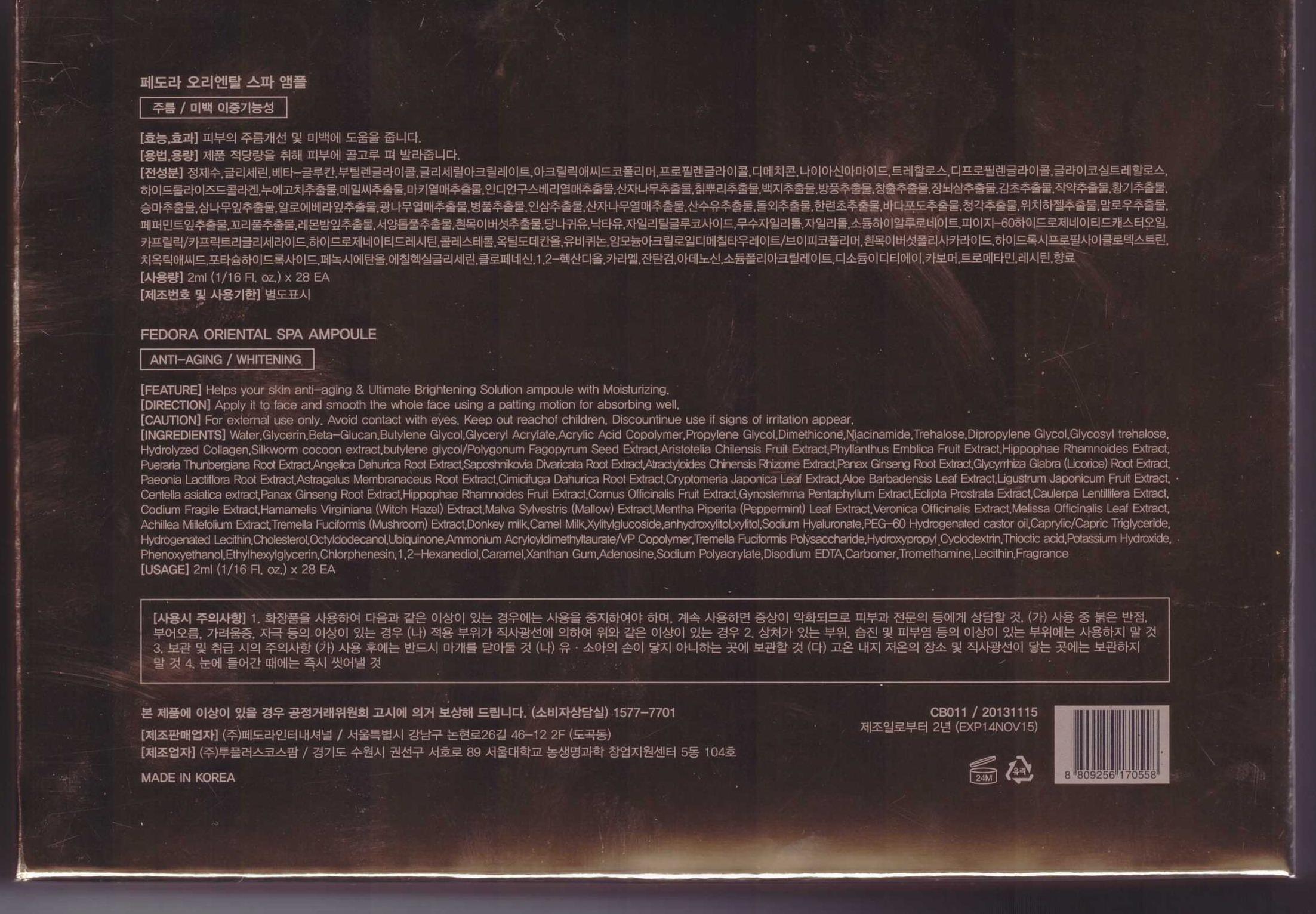 DRUG LABEL: FEDORA Oriental Spa Ampoule
NDC: 62620-1001 | Form: LIQUID
Manufacturer: Fedora International Co., Ltd.
Category: otc | Type: HUMAN OTC DRUG LABEL
Date: 20140306

ACTIVE INGREDIENTS: GLYCERIN 0.0798 g/1 mL
INACTIVE INGREDIENTS: WATER; HYALURONATE SODIUM; BUTYLENE GLYCOL; BETAINE

Drug Facts

ACTIVE INGREDIENT

glycerin

INACTIVE INGREDIENT

Water, Glycerin, Beta-Glucan, Butylene Glycol, Glyceryl Acrylate, Acrylic Acid Copolymer, Propylene Glycol, Dimethicone, Niacinamide, Trehalose, Dipropylene Glycol, Glycosyl trehalose, Hydrolyzed Collagen, Silkworm cocoon extract, butylene glycol/Polygonum Fagopyrum Seed Extract, Aristotelia Chilensis Fruit Extract, Phyllanthus Emblica Fruit Extract, Hippophae Rhamnoides Extract, Pueraria Thunbergiana Root Extract, Angelica Dahurica Root Extract, Saposhnikovia Divaricata Root Extract, Atractyloides Chinensis Rhizome Extract, Panax Ginseng Root Extract, Glycyrrhiza Glabra (Licorice) Root Extract, Paeonia Lactiflora Root Extract, Astragalus Membranaceus Root Extract, Cimicifuga Dahurica Root Extract, Cryptomeria Japonica Leaf Extract, Aloe Barbadensis Leaf Extract, Ligustrum Japonicum Fruit Extract, Centella asiatica extract, Panax Ginseng Root Extract, Hippophae Rhamnoides Fruit Extract, Cornus Officinalis Fruit Extract, Gynostemma Pentaphyllum Extract, Eclipta Prostrata Extract, Caulerpa Lentillifera Extract, Codium Fragile Extract, Hamamelis Virginiana (Witch Hazel) Extract, Malva Sylvestris (Mallow) Extract, Mentha Piperita (Peppermint) Leaf Extract, Veronica Officinalis Extract, Melissa Officinalis Leaf Extract, Achillea Millefolium Extract, Tremella Fuciformis (Mushroom) Extract, Donkey milk, Camel Milk, Xylitylglucoside, anhydroxylitol, xylitol, Sodium Hyaluronate, PEG-60 Hydrogenated castor oil, Caprylic/Capric Triglyceride, Hydrogenated Lecithin, Cholesterol, Octyldodecanol, Ubiquinone, Ammonium Acryloyldimethyltaurate/VP Copolymer, Tremella Fuciformis Polysaccharide, Hydroxypropyl Cyclodextrin, Thioctic acid, Potassium Hydroxide, Phenoxyethanol, Ethylhexylglycerin, Chlorphenesin, 1,2-Hexanediol, Caramel, Xanthan Gum, Adenosine, Sodium Polyacrylate, Disodium EDTA, Carbomer, Tromethamine, Lecithin, Fragrance

PURPOSE

helps your skin anti-aging and ultimate brightening solution ampoule with moisturizing

keep out of reach of the children

INDICATIONS AND USAGE

apply it to face and smooth the whole face using a patting motion for absorbing well

WARNINGS

avoid contact with eyes
discontinue use if signs of irritation appear

DOSAGE AND ADMINISTRATION

for external use only